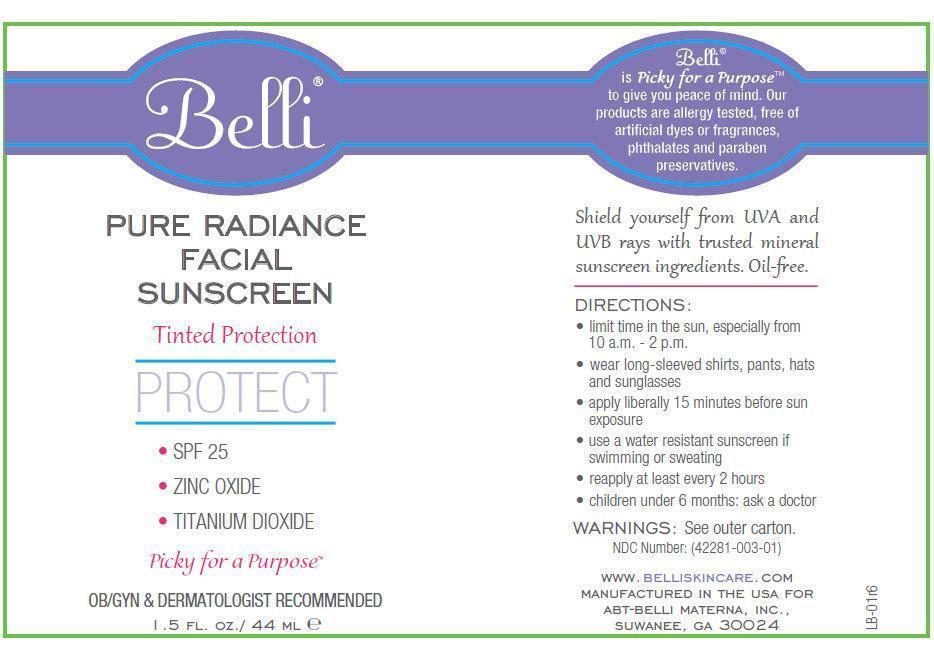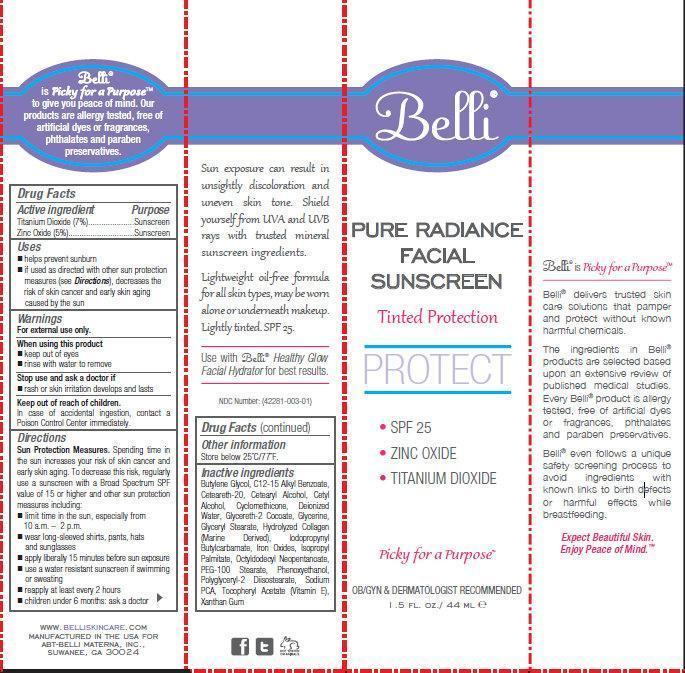 DRUG LABEL: Belli Pure Radiance Facial Sunscreen Tinted Protection SPF 25
NDC: 42281-003 | Form: CREAM
Manufacturer: BODY HALO LLC
Category: otc | Type: HUMAN OTC DRUG LABEL
Date: 20250129

ACTIVE INGREDIENTS: TITANIUM DIOXIDE 70 mg/1 mL; ZINC OXIDE 50 mg/1 mL
INACTIVE INGREDIENTS: BUTYLENE GLYCOL; ALKYL (C12-15) BENZOATE; POLYOXYL 20 CETOSTEARYL ETHER; CETOSTEARYL ALCOHOL; CETYL ALCOHOL; CYCLOMETHICONE; WATER; GLYCERETH-2 COCOATE; GLYCERIN; GLYCERYL MONOSTEARATE; MARINE COLLAGEN, SOLUBLE; IODOPROPYNYL BUTYLCARBAMATE; FERRIC OXIDE RED; ISOPROPYL PALMITATE; OCTYLDODECYL NEOPENTANOATE; PEG-100 STEARATE; PHENOXYETHANOL; POLYGLYCERYL-2 DIISOSTEARATE; SODIUM PYRROLIDONE CARBOXYLATE; .ALPHA.-TOCOPHEROL ACETATE; XANTHAN GUM

BODY HALO - Belli - Pure Radiance Facial Sunscreen Tinted Protection SPF 25 (42281-003)

Active ingredient

Titanium Dioxide (7%)
Zinc Oxide (5%)

Purpose

Sunscreen

Uses

- helps prevent sunburn
- if used as directed with other sun protection measures (see Directions), decreases the risk of skin cancer and early skin aging caused by the sun

Warnings

For external use only.

When using this product

- keep out of eyes
- rinse with water to remove

Stop use and ask a doctor if

- rash or skin irritation develops and lasts

Keep out of reach of children.

In case of accidental ingestion, contact a Poison Control Center immediately.

Directions

Sun Protection Measures.Spending time in the sun increases your risk of skin cancer and early skin aging. To decrease this risk, regularly use a sunscreen with a Broad Spectrum SPF value of 15 or higher and other sun protection measures including:

- limit time in the sun, especially from 10 a.m. - 2 p.m.
- wear long-sleeved shirts, pants, hats and sunglasses
- apply liberally 15 minutes before sun exposure
- use a water resistant sunscreen if swimming or sweating
- reapply at least every 2 hours
- children under 6 months: ask a doctor

Other information

Store below 25 degree C/77 degree F.

Inactive ingredients

Butylene Glycol, C12-15 Alkyl Benzoate, Cetearyl Alcohol, Cetyl Alcohol, Cyclomethicone, Deionized Water, Glycereth-2 Cocoate, Glycerine, Glyceryl Stearate, Hydrolyzed Collagen (Marine Derived) Iodopropynyl Butylcarbamate, Iron Oxides, Isopropyl Palmitate, Octyldodecyl Neopentanoate, PEG-100 Stearate, Phenoxyethanol, Polyglyceryl-2 Diisostearate, Sodium PCA, Tocopheryl Acetate (Vitamin E), Xanthan Gum